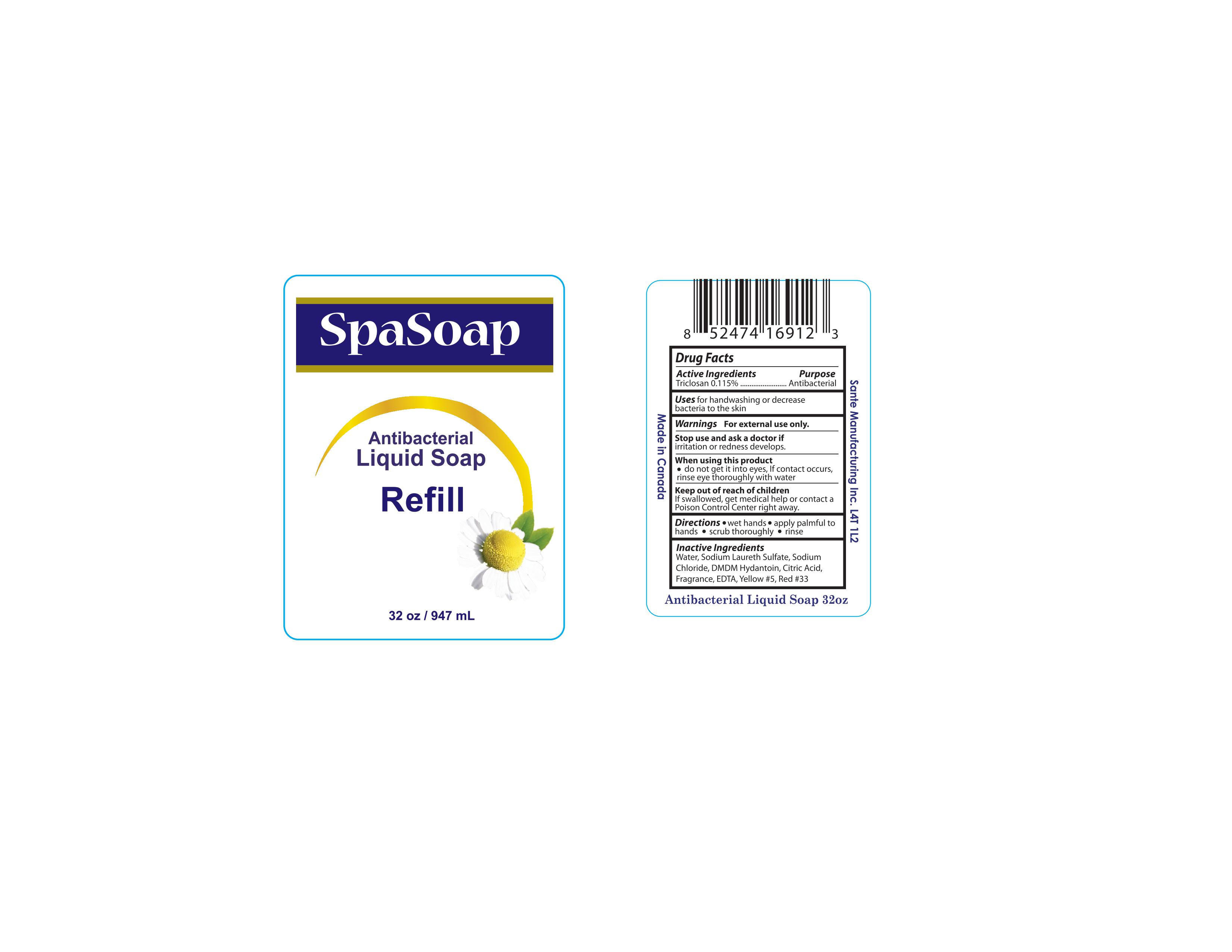 DRUG LABEL: Triclosan
NDC: 50157-119 | Form: SOAP
Manufacturer: Brands International
Category: otc | Type: HUMAN OTC DRUG LABEL
Date: 20160530

ACTIVE INGREDIENTS: TRICLOSAN 1.15 mg/1 mL
INACTIVE INGREDIENTS: WATER; SODIUM LAURETH SULFATE; SODIUM CHLORIDE; EDETIC ACID; FD&C YELLOW NO. 5; D&C RED NO. 33; DMDM HYDANTOIN; ANHYDROUS CITRIC ACID

Antibacterial Liquid Soap Refill

Drug Facts

Active Ingredients

Triclosan 0.115%

Purpose

Antibacterial

Uses

for handwashing or decrease bacteria to the skin

WARNINGS

For external use only

Stop use and ask a doctor if

irritation or redness develops

When using this product

- do not get it into eyes, if contact occurs, rinse eye thoroughly with water

Keep out of reach of children

If swallowed, get medical help or contact a Poison Control Center right away

Directions

- Wet hands
- apply palmful to hands
- scrub throughly
- rinse

Inactive Ingredients

Water, Sodium Laureth Sulfate, Sodium Chloride, DMDM Hydantoin, Citric Acid, Fragrance, EDTA, Yellow #5, Red# 33

Package Label

Spa Soap

Antibacterial

Liquid Soap

Refill